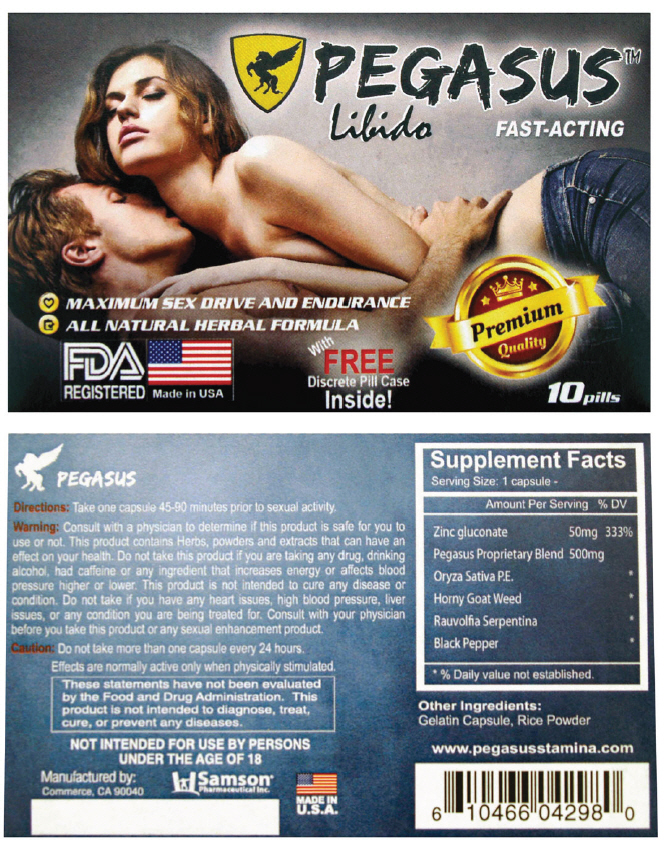 DRUG LABEL: Pegasus Male Sexual Enhancer
NDC: 20146-1002 | Form: CAPSULE
Manufacturer: SAMSON PHARMACEUTICAL
Category: other | Type: DIETARY SUPPLEMENT
Date: 20160408

ACTIVE INGREDIENTS: Zinc Gluconate 50 mg/1 1
INACTIVE INGREDIENTS: Brown Rice; Icariin; Rauwolfia Serpentina; Black Pepper

Pegasus™ Male Sexual Enhancer

Directions

Take one capsule 45-90 minutes prior to sexual activity.

Warning

Consult with a physician to determine if this product is safe for you to use or not. This product contains Herbs, powders and extracts that can have an effect on your health. Do not take this product if you are taking any drug, drinking alcohol, had caffeine or any ingredient that increases energy or affects blood pressure higher or lower. This product is not intended to cure any disease or condition. Do not take if you have any heart issues, high blood pressure, liver issues, or any condition you are being treated for. Consult with your physician before you take this product or any sexual enhancement product.

Caution

Do not take more than one capsule every 24 hours.

These statements have not been evaluated by the Food and Drug Administration. This product is not intended to diagnose, treat, cure, or prevent any diseases. Not intended for use by person under the age of 18.

HEALTH CLAIM

Supplement Facts
Serving Size: 1 capsule
Amount Per Serving |  | % DV
Zinc gluconate | 50mg | 333%
Pegasus Proprietary Blend | 500mg
Oryza Sativa P.E. |  | [% Daily value not established.]
Horny Goat Weed
White Willow Bark
Rauvolfia Serpentina
Black Pepper

Other Ingredients

Gelatin Capsule, Rice Powder

HEALTH CLAIM

Manufactured by:
Samson Pharmaceutical Inc.
Commerce, CA 90040

PRINCIPAL DISPLAY PANEL - 10 Capsule Blister Pack Box

PEGASUS™
Libido
FAST-ACTING

• MAXIMUM SEX DRIVE AND ENDURANCE
• ALL NATURAL HERBAL FORMULA

Premium
Quality

FDA
REGISTERED

Made in USA

With
FREE
Discrete Pill Case
Inside!

10pills